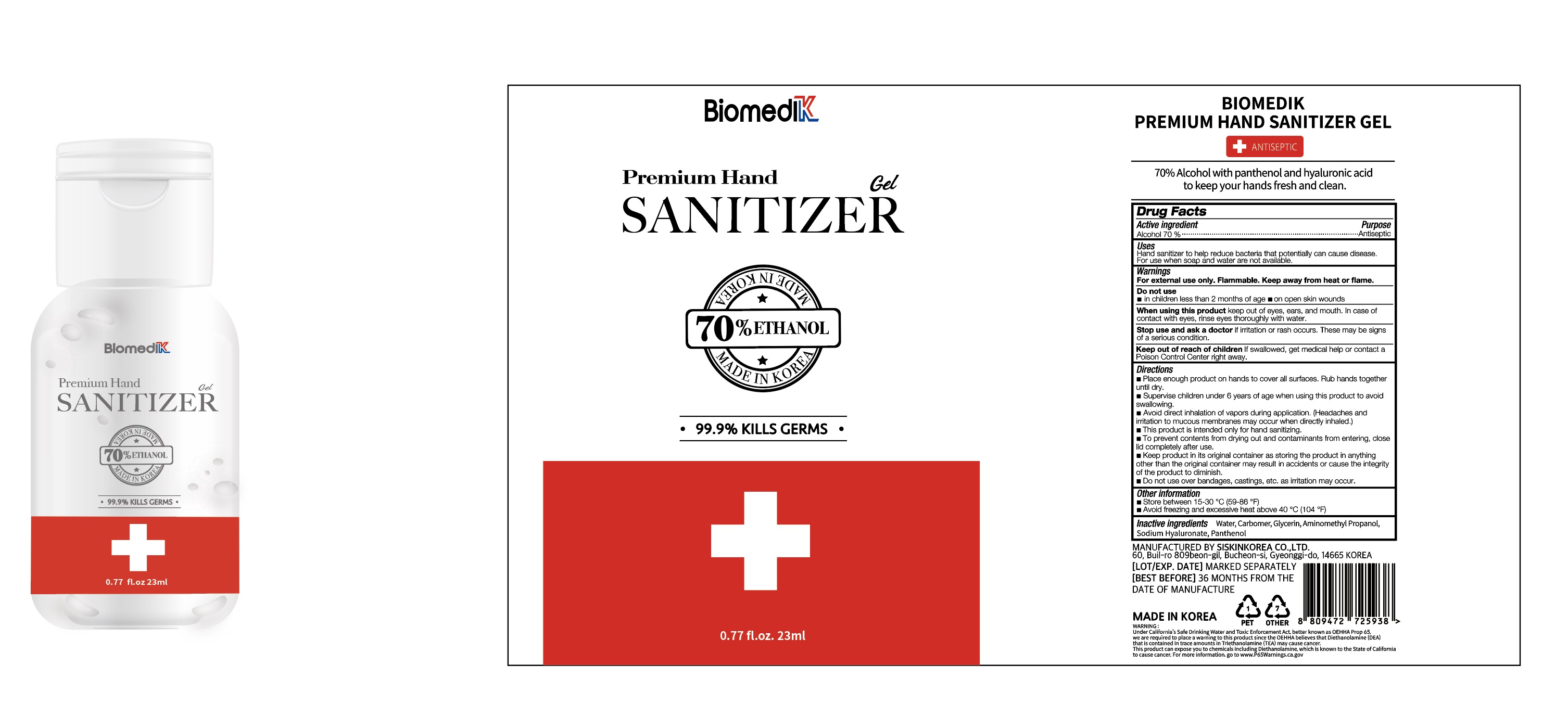 DRUG LABEL: BIOMEDIK Premium Hand Sanitizer Gel
NDC: 74514-7023 | Form: GEL
Manufacturer: SISKINKOREA CO.,LTD.
Category: otc | Type: HUMAN OTC DRUG LABEL
Date: 20200614

ACTIVE INGREDIENTS: ALCOHOL 16.1 mL/23 mL
INACTIVE INGREDIENTS: GLYCERIN; AMINOMETHYLPROPANOL; PANTHENOL; WATER; HYALURONATE SODIUM; CARBOMER HOMOPOLYMER, UNSPECIFIED TYPE

BIOMEDIK Premium Hand Sanitizer Gel [74514-7023-1] 23 mL, Bottle+Cap